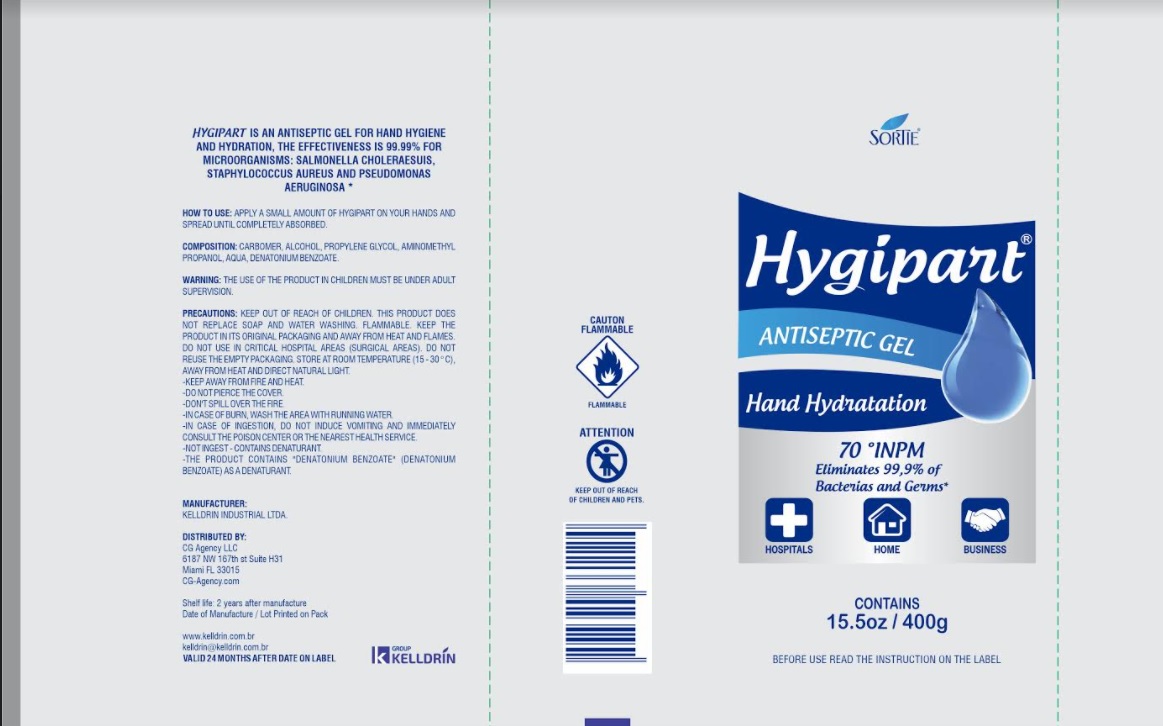 DRUG LABEL: HYGIPART ANTISEPTC
NDC: 80214-004 | Form: GEL
Manufacturer: MOD DESIGN BUILD
Category: otc | Type: HUMAN OTC DRUG LABEL
Date: 20210326

ACTIVE INGREDIENTS: ALCOHOL 70 g/100 g
INACTIVE INGREDIENTS: WATER; CARBOMER HOMOPOLYMER, UNSPECIFIED TYPE; PROPYLENE GLYCOL; AMINOMETHYLPROPANOL; DENATONIUM BENZOATE

Active Ingredient

Alcohol 70%

Purpose

Antiseptic gel

Use

Hygipart is an antiseptic gel for hand hygiene and hydration, the effectiveness is 99,99% for
microorganisms: Salmonella choleraesuis, Staphylococcus aureus and Pseudomonas aeruginosa.

Warnings

Keep out of reach of children.
- This product does not replace soap and water washing.
- Flammable.
- Keep the product in its original packaging and away from heat and flames.
- Do not use in critical hospital areas (surgical areas).
- Do not reuse the empty packaging.
-Store at room temperature (15- 30°C}, away from heat and direct natural light.
- Keep away from fire and heat.
- Do not pierce the cover.
- Don't spill over the fire.
-In case of burn, wash the area with running water.
- In case of ingestion, do not induce vomiting and immediately consult the poison center or the
nearest health service.
- Not ingest- contains denaturant.
-The product contains "Denatonium Benzoate" as a denaturant.

Directions

Apply a small amount of Hygipart on your hands and spread until completely absorbed.

Inactive ingredients

CARBOMER, ALCOHOL, PROPYLENE GLYCOL, AMINOMETHYL PROPANOL, AQUA, DENATONIUM
BENZOATE.